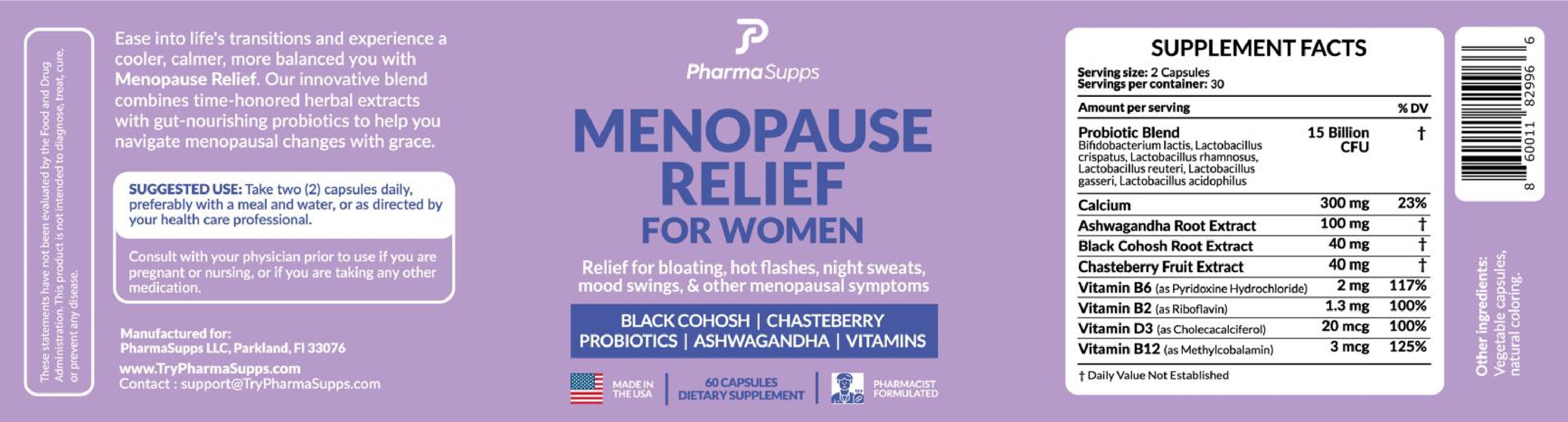 DRUG LABEL: Menopause Relief for Women
NDC: 87260-002 | Form: CAPSULE
Manufacturer: PharmaSupps LLP
Category: other | Type: Dietary Supplement
Date: 20260116

ACTIVE INGREDIENTS: BLACK COHOSH 40 mg/1 1; CHASTE TREE FRUIT 40 mg/1 1; PYRIDOXINE 2 mg/1 1; RIBOFLAVIN 1.3 mg/1 1; CHOLECALCIFEROL 20 ug/1 1; CYANOCOBALAMIN 3 ug/1 1

Menopause Relief for Women

STATEMENT OF IDENTITY

This statement have not been evaluated by the Food and Drug Administration. This product is not intended to diagnose, treat, cure or prevent any disease.